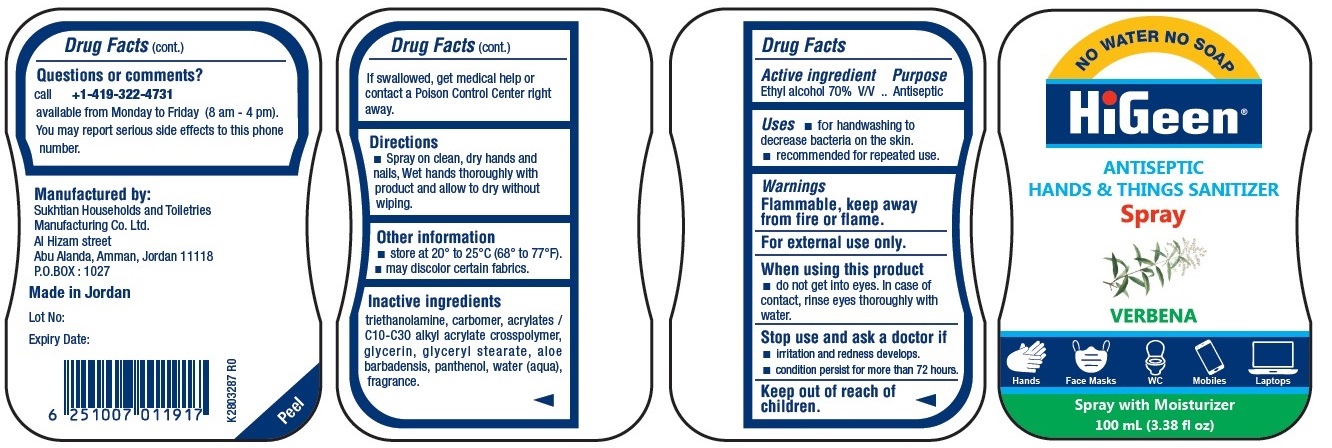 DRUG LABEL: HiGeen ANTISEPTIC HANDS AND THINGS SANITIZER VERBENA
NDC: 71490-047 | Form: SPRAY
Manufacturer: SUKHTIAN-HTM ( HOUSEHOLDS & TOILETRIES MFG.CO)
Category: otc | Type: HUMAN OTC DRUG LABEL
Date: 20211028

ACTIVE INGREDIENTS: ALCOHOL 70 mL/100 mL
INACTIVE INGREDIENTS: TROLAMINE; CARBOMER HOMOPOLYMER, UNSPECIFIED TYPE; CARBOMER INTERPOLYMER TYPE A (ALLYL SUCROSE CROSSLINKED); GLYCERIN; GLYCERYL MONOSTEARATE; ALOE VERA LEAF; PANTHENOL; WATER

HiGeen® ANTISEPTIC HANDS & THINGS SANITIZER SPRAY VERBENA

Active ingredient

Ethyl alcohol 70% V/V

Purpose

Antiseptic

Uses

• for hand washing to decrease bacteria on the skin.
• recommended for repeated use.

Warnings

Flammable, keep away from fire or flame.
For external use only.

When using this product
• do not get into eyes. In case of contact, rinse eyes thoroughly with water.

Stop use and ask a doctor if
• irritation and redness develops.
• condition persist for more than 72 hours.

Keep out of reach of children.
If swallowed, get medical help or contact a Poison Control Center right away.

Directions

• Spray on clean, dry hands and nails, Wet hands thoroughly with product and allow to dry without wiping

Other information

• store at 20° to 25°C (68° to 77°F).
• may discolor certain fabrics.

Inactive ingredients

triethanolamine, carbomer, acrylates /C10-C30 alkyl acrylate crosspolymer, glycerin, glyceryl stearate, aloe barbadensis, panthenol, water (aqua),
fragrance.

Questions or comments?

call +1-419-322-4731
available from Monday to Friday (8 am - 4 pm).
You may report serious side effects to this phone number.

NO WATER NO SOAP

Hands Face Masks WC Mobiles Laptops

Spray with Moisturizer

Manufactured by:
Sukhtian Households and Toiletries Manufacturing Co. Ltd.
Al Hizam street
Abu Alanda, Amman, Jordan 11118
P.O.BOX : 1027

Made in Jordan